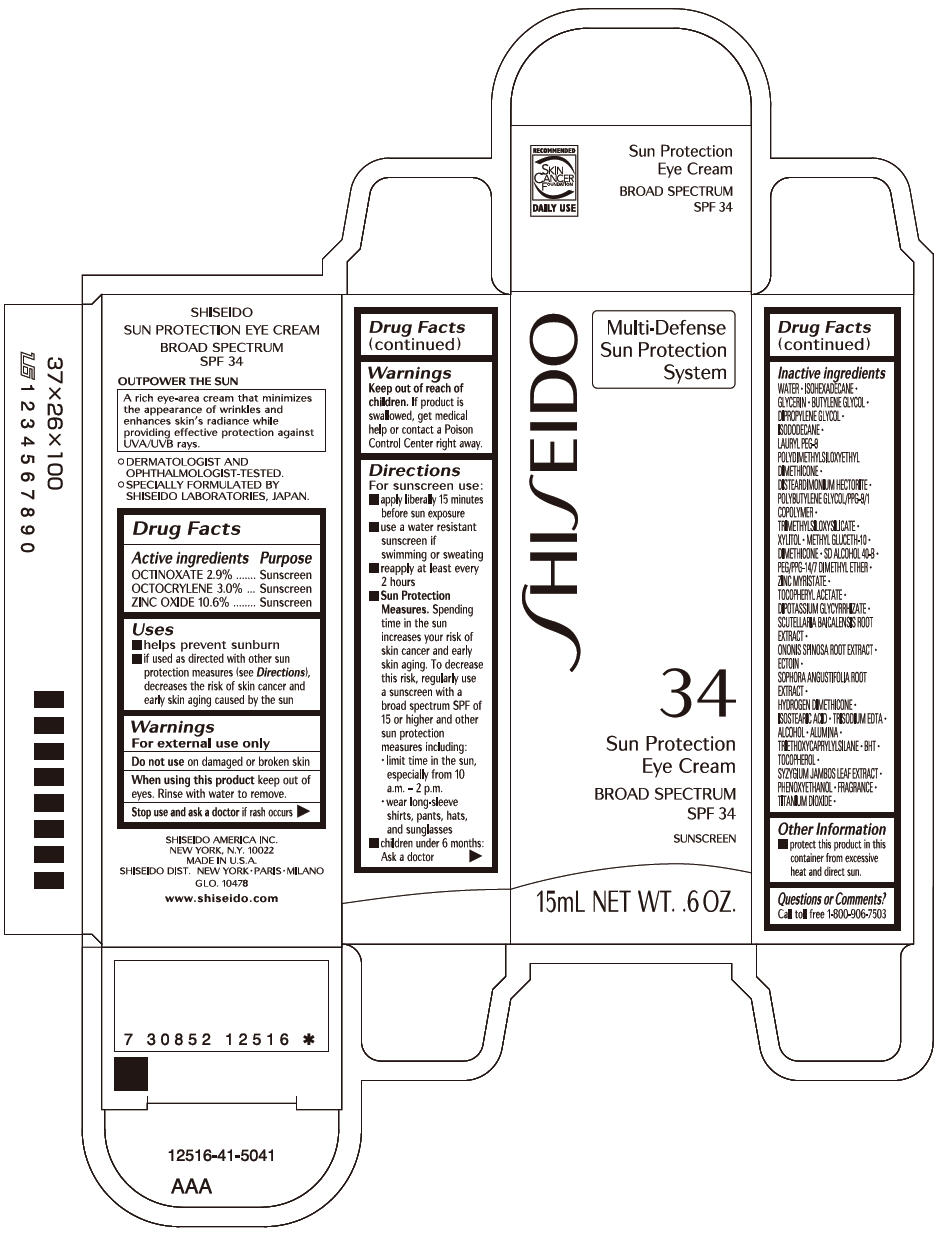 DRUG LABEL: SHISEIDO SUN PROTECTION EYE
NDC: 52686-335 | Form: CREAM
Manufacturer: SHISEIDO AMERICA INC.
Category: otc | Type: HUMAN OTC DRUG LABEL
Date: 20231227

ACTIVE INGREDIENTS: OCTINOXATE 479 mg/16.5 g; OCTOCRYLENE 495 mg/16.5 g; ZINC OXIDE 1749 mg/16.5 g
INACTIVE INGREDIENTS: WATER; ISOHEXADECANE; GLYCERIN; BUTYLENE GLYCOL; DIPROPYLENE GLYCOL; ISODODECANE; TRIMETHYLSILOXYSILICATE (M/Q 0.6-0.8); XYLITOL; METHYL GLUCETH-10; DIMETHICONE; PEG/PPG-14/7 DIMETHYL ETHER; ZINC MYRISTATE; .ALPHA.-TOCOPHEROL ACETATE, DL-; GLYCYRRHIZINATE DIPOTASSIUM; SCUTELLARIA BAICALENSIS ROOT; ONONIS SPINOSA ROOT; ECTOINE; SOPHORA FLAVESCENS ROOT; ISOSTEARIC ACID; EDETATE TRISODIUM; ALCOHOL; ALUMINUM OXIDE; TRIETHOXYCAPRYLYLSILANE; BUTYLATED HYDROXYTOLUENE; .ALPHA.-TOCOPHEROL; SYZYGIUM JAMBOS LEAF; PHENOXYETHANOL; TITANIUM DIOXIDE

SHISEIDO SUN PROTECTION EYE CREAM

Drug Facts

ACTIVE INGREDIENT

ACTIVE INGREDIENTS: | Purpose
OCTINOXATE 2.9% | Sunscreen
OCTOCRYLENE 3.0% | Sunscreen
ZINC OXIDE 10.6% | Sunscreen

Uses

- helps prevent sunburn
- if used as directed with other sun protection measures (see Directions), decreases the risk of skin cancer and early skin aging caused by the sun

Warnings

For external use only

Do not use on damaged or broken skin

When using this product keep out of eyes. Rinse with water to remove.

Stop use and ask a doctor if rash occurs

Keep out of reach of children. If product is swallowed, get medical help or contact a Poison Control Center right away.

Directions

For sunscreen use:

- apply liberally 15 minutes before sun exposure
- use a water resistant sunscreen if swimming or sweating
- reapply at least every 2 hours
- Sun Protection Measures. Spending time in the sun increases your risk of skin cancer and early skin aging. To decrease this risk, regularly use a sunscreen with a broad spectrum SPF of 15 or higher and other sun protection measures including:
  - limit time in the sun, especially from 10 a.m. – 2 p.m.
  - wear long-sleeve shirts, pants, hats, and sunglasses
- children under 6 months: Ask a doctor

Inactive Ingredients

WATER • ISOHEXADECANE • GLYCERIN • BUTYLENE GLYCOL • DIPROPYLENE GLYCOL • ISODODECANE • LAURYL PEG-9 POLYDIMETHYLSILOXYETHYL DIMETHICONE • DISTEARDIMONIUM HECTORITE • POLYBUTYLENE GLYCOL/PPG-9/1 COPOLYMER • TRIMETHYLSILOXYSILICATE • XYLITOL • METHYL GLUCETH-10 • DIMETHICONE • SD ALCOHOL 40-B • PEG/PPG-14/7 DIMETHYL ETHER • ZINC MYRISTATE • TOCOPHERYL ACETATE • DIPOTASSIUM GLYCYRRHIZATE • SCUTELLARIA BAICALENSIS ROOT EXTRACT • ONONIS SPINOSA ROOT EXTRACT • ECTOIN • SOPHORA ANGUSTIFOLIA ROOT EXTRACT • HYDROGEN DIMETHICONE • ISOSTEARIC ACID • TRISODIUM EDTA • ALCOHOL • ALUMINA • TRIETHOXYCAPRYLYLSILANE • BHT • TOCOPHEROL • SYZYGIUM JAMBOS LEAF EXTRACT • PHENOXYETHANOL • FRAGRANCE • TITANIUM DIOXIDE •

Other information

- protect this product in this container from excessive heat and direct sun.

Questions or comments?

Call toll free 1-800-906-7503

PRINCIPAL DISPLAY PANEL - 15mL Tube Carton

SHISEIDO

Multi-Defense
Sun Protection
System

34

Sun Protection
Eye Cream

BROAD SPECTRUM
SPF 34

SUNSCREEN

15mL NET WT. .6 OZ.